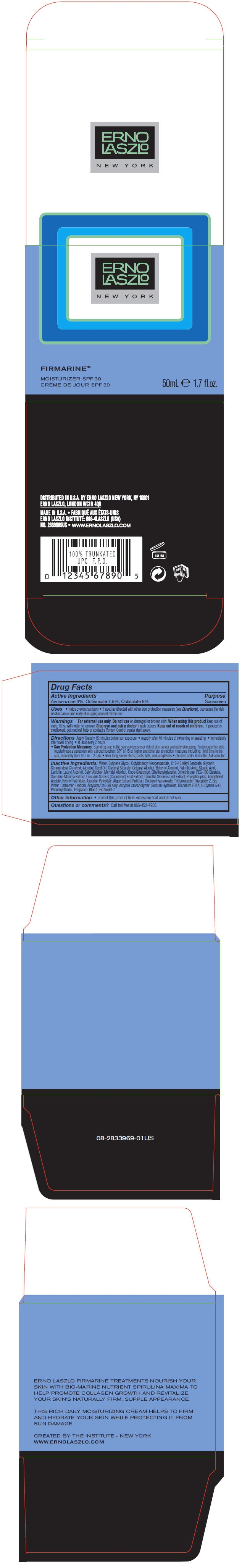 DRUG LABEL: FIRMARINE MOISTURIZER SPF 30
NDC: 59735-480 | Form: CREAM
Manufacturer: MANA PRODUCTS, INC.
Category: otc | Type: HUMAN OTC DRUG LABEL
Date: 20240103

ACTIVE INGREDIENTS: OCTISALATE 5 g/100 g; AVOBENZONE 3 g/100 g; OCTINOXATE 7.5 g/100 g
INACTIVE INGREDIENTS: LAURYL ALCOHOL; COCO GLUCOSIDE; DIMETHICONE; PEG-100 STEARATE; CUCUMBER; OCTYLDODECYL NEOPENTANOATE; ALKYL (C12-15) BENZOATE; GLYCERIN; JOJOBA OIL; WATER; BUTYLENE GLYCOL; GLYCERYL MONOSTEARATE; CETOSTEARYL ALCOHOL; DOCOSANOL; PALMITIC ACID; STEARIC ACID; CETYL ALCOHOL; MYRISTYL ALCOHOL; .ALPHA.-TOCOPHEROL ACETATE; VITAMIN A PALMITATE; SODIUM CHLORIDE; SODIUM HYDROXIDE; EDETATE DISODIUM; PHENOXYETHANOL; FD&C BLUE NO. 1; EXT. D&C VIOLET NO. 2; ETHYLHEXYLGLYCERIN; SPIRULINA MAXIMA; GREEN TEA LEAF; ASCORBYL PALMITATE; PULLULAN; O-CYMEN-5-OL; HYALURONATE SODIUM

FIRMARINE MOISTURIZER SPF 30

Active Ingredients

Avobenzone 3%, Octinoxate 7.5%, Octisalate 5%

Purpose

Sunscreen

Uses

- helps prevent sunburn
- if used as directed with other sun protection measures (see Directions), decreases the risk of skin cancer and early skin aging caused by the sun

Warnings

- For external use only.
- Do not use on damaged or broken skin.
- When using this product keep out of eyes. Rinse with water to remove.

Directions

Apply liberally 15 minutes before sun exposure

- reapply: after 40 minutes of swimming or sweating
- immediately after towel drying
- at least every 2 hours
- Sun Protection Measures. Spending time in the sun increases your risk of skin cancer and early skin aging. To decrease this risk, regularly use a sunscreen with a broad spectrum SPF of 15 or higher and other sun protection measures including: limit time in the sun, especially from 10 a.m. - 2 p.m.
- wear long-sleeve shirts, pants, hats, and sunglasses
- children under 6 months: Ask a doctor

Inactive Ingredients

Water, Butylene Glycol, Octyldodecyl Neopentanoate, C12-15 Alkyl Benzoate, Glycerin, Simmondsia Chinensis (Jojoba) Seed Oil, Glyceryl Stearate, Cetearyl Alcohol, Behenyl Alcohol, Palmitic Acid, Stearic Acid, Lecithin, Lauryl Alcohol, Cetyl Alcohol, Myristyl Alcohol, Coco-Glucoside, Ethylhexylglycerin, Dimethicone, PEG-100 Stearate, Spirulina Maxima Extract, Cucumis Sativus (Cucumber) Fruit Extract, Camellia Sinensis Leaf Extract, Phospholipids, Tocopheryl Acetate, Retinyl Palmitate, Ascorbyl Palmitate, Algae Extract, Pullulan, Sodium Hyaluronate, Trifluoroacetyl Tripeptide-2, Sea Water, Carbomer, Dextran, Acrylates/C10-30 Alkyl Acrylate Crosspolymer, Sodium Hydroxide, Disodium EDTA, O-Cymen-5-Ol, Phenoxyethanol, Fragrance, Blue 1, Ext Violet 2.

Other information

protect this product from excessive heat and direct sun

Questions or comments?

Call toll free at 866-452-7956

Stop use and ask a doctor if rash occurs.

RECENT MAJOR CHANGES

dosage & admin update

Keep out of reach of children. If product is swallowed, get medical help or contact a Poison Control Center right away.